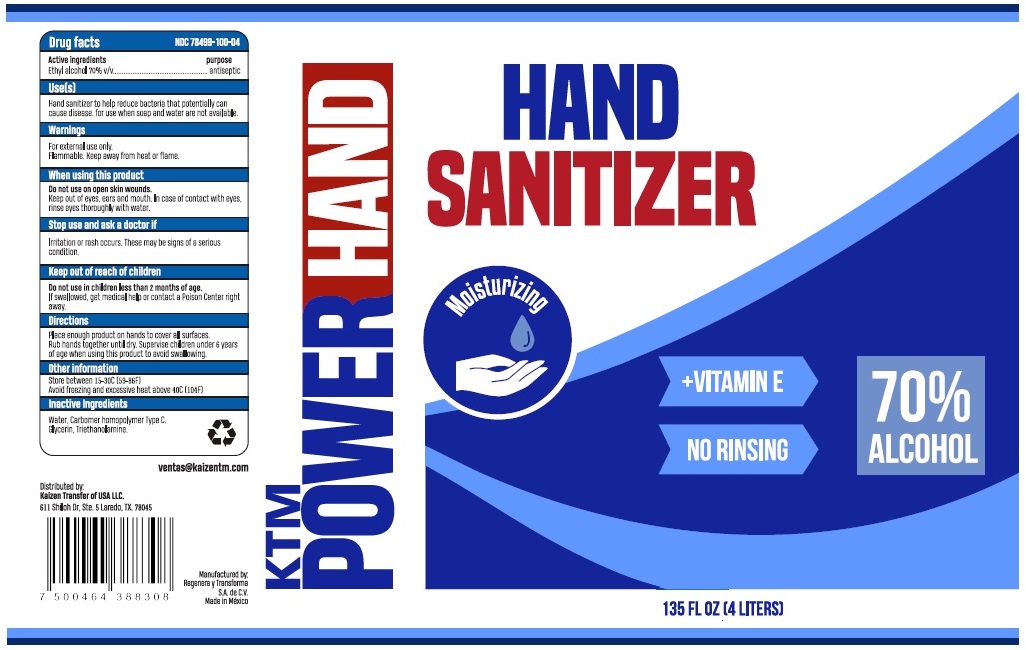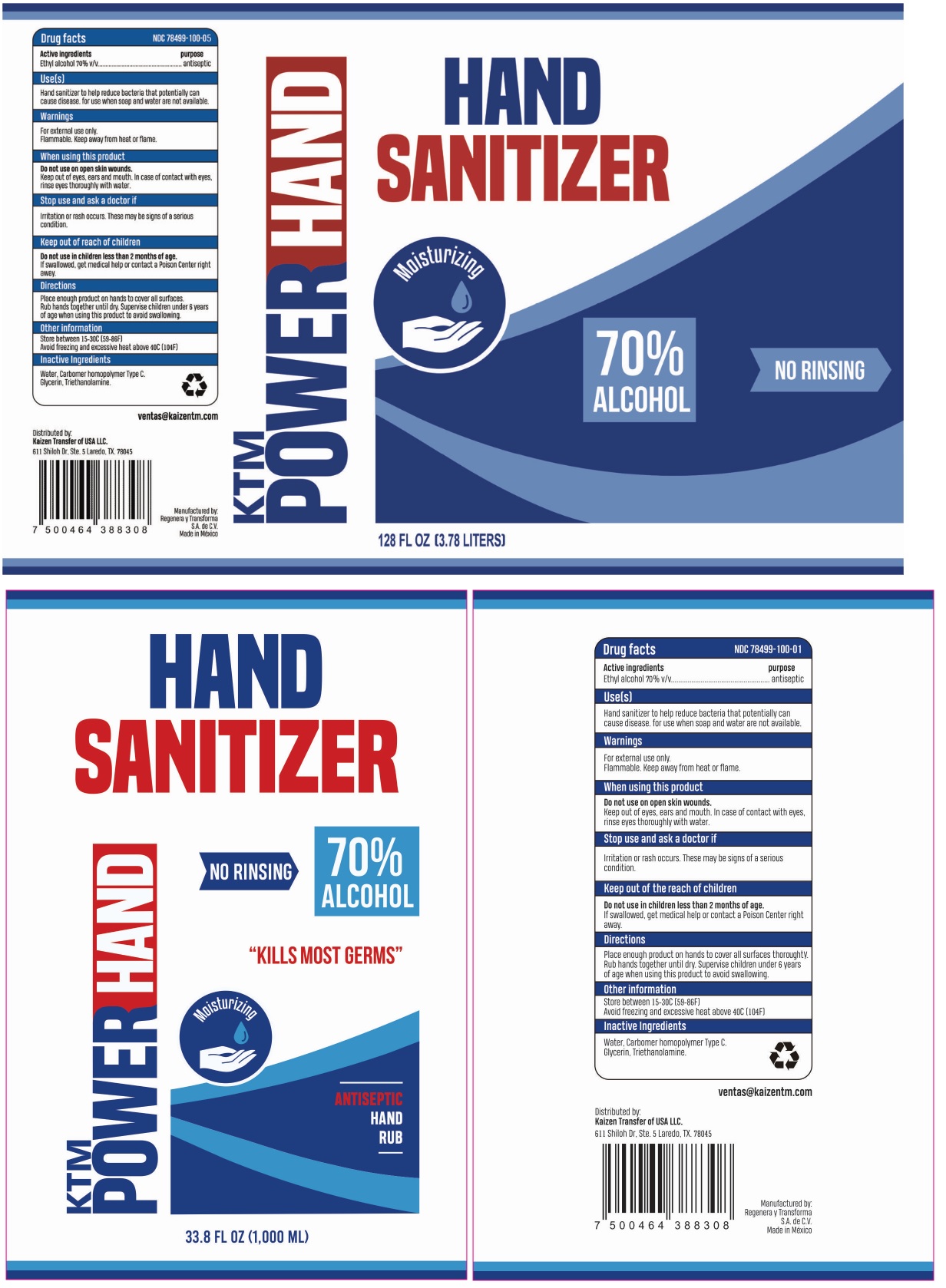 DRUG LABEL: KTM power hand
NDC: 78499-100 | Form: GEL
Manufacturer: Regenera y Transforma, S.A. de C.V.
Category: otc | Type: HUMAN OTC DRUG LABEL
Date: 20200625

ACTIVE INGREDIENTS: ALCOHOL 70 mL/100 mL
INACTIVE INGREDIENTS: WATER; CARBOMER HOMOPOLYMER TYPE C (ALLYL PENTAERYTHRITOL CROSSLINKED); GLYCERIN; TROLAMINE

KTM POWER HAND HAND SANITIZER

Active ingredients

Ethyl alcohol 70% v/v

purpose

antiseptic

Use[s]

Hand sanitizer to help reduce bacteria that potentially can cause disease. for use when soap and water are not available.

Warnings

For external use only.

Flammable. Keep away from heat or flame.

When using this product

Do not use on open skin wounds.

Keep out of eyes, ears, and mouth. In case of contact with eyes, rinse eyes thoroughly with water.

Stop use and ask a doctor if

Irritation or rash occurs. These may be signs of a serious condition.

Keep out of reach of children

Do not use in children less than 2 months of age.

If swallowed, get medical help or contact a Poison Center right away.

Directions

Place enough product on hands to cover all surfaces thoroughly. Rub hands together until dry. Supervise children under 6 years of age when using this product to avoid swallowing.

Other information

Store between 15-30C (59-86F)

Avoid freezing and excessive heat above 40C (104F)

Inactive Ingredients

Water, Carbomer homopolymer Type C, Glycerin, Triethanolamine.

NO RINSING

70% ALCOHOL

"KILLS THE MOST GERMS"

Moisturizing

ANTISEPTIC

HAND RUB

ventas@kaizentm.com

Distributed by:

Kaizen Transfer of USA LLC.

611 Shiloh Dr, Ste. 5 Laredo, TX. 78045

Manufactured by:

Regenera y Transforma S.A.de C.V.

Made in México